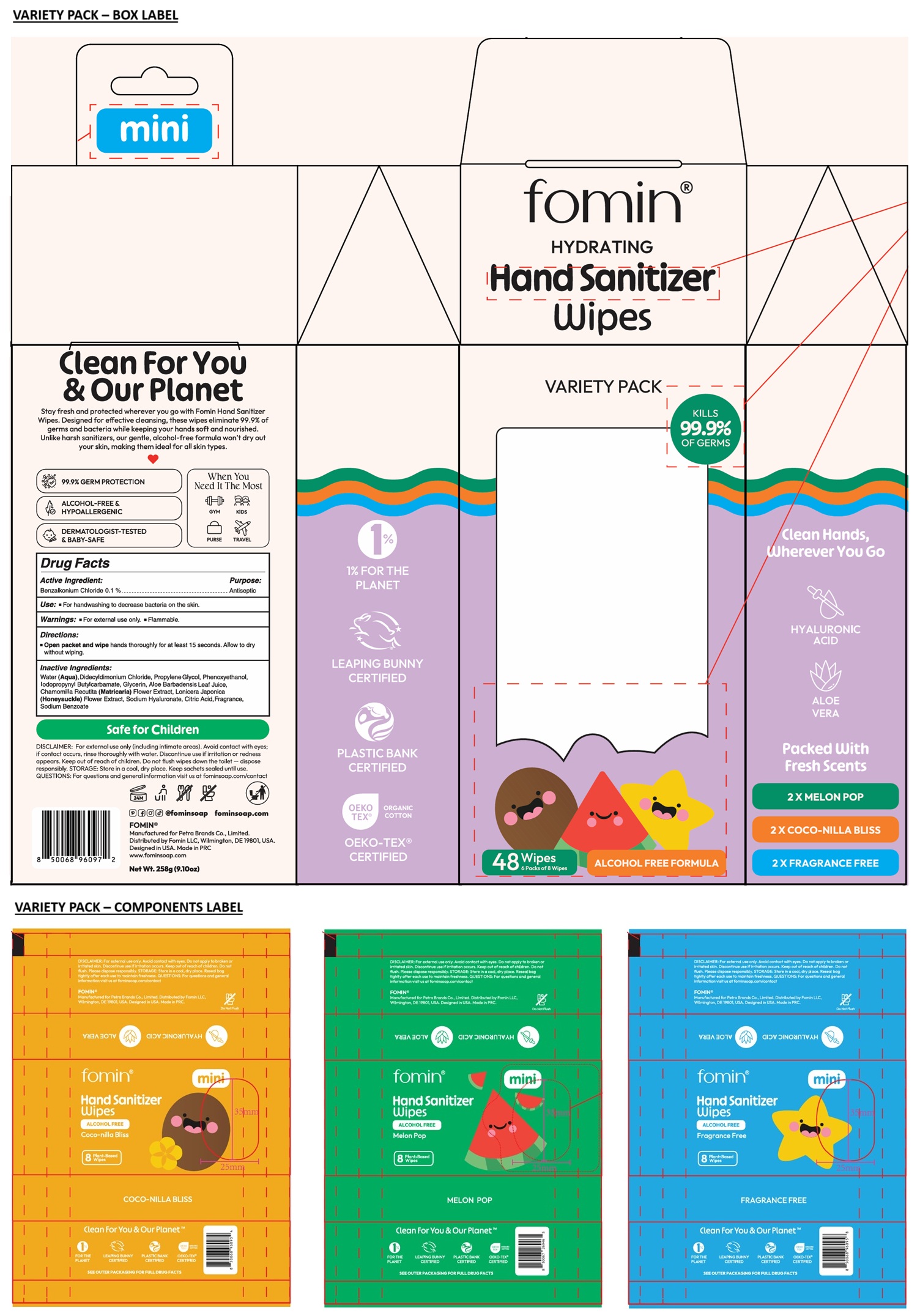 DRUG LABEL: fomin mini Hand Sanitizer Wipes - 6 - VARIETY PACK
NDC: 85755-004 | Form: KIT | Route: TOPICAL
Manufacturer: Fomin LLC
Category: otc | Type: HUMAN OTC DRUG LABEL
Date: 20250703

ACTIVE INGREDIENTS: BENZALKONIUM CHLORIDE 0.1 g/100 mL; BENZALKONIUM CHLORIDE 0.1 g/100 mL; BENZALKONIUM CHLORIDE 0.1 g/100 mL
INACTIVE INGREDIENTS: WATER; DIDECYLDIMONIUM CHLORIDE; PROPYLENE GLYCOL; PHENOXYETHANOL; IODOPROPYNYL BUTYLCARBAMATE; GLYCERIN; ALOE VERA LEAF JUICE; CHAMOMILE; LONICERA JAPONICA FLOWER; HYALURONATE SODIUM; CITRIC ACID MONOHYDRATE; SODIUM BENZOATE; WATER; DIDECYLDIMONIUM CHLORIDE; PROPYLENE GLYCOL; PHENOXYETHANOL; IODOPROPYNYL BUTYLCARBAMATE; GLYCERIN; ALOE VERA LEAF JUICE; CHAMOMILE; LONICERA JAPONICA FLOWER; HYALURONATE SODIUM; CITRIC ACID MONOHYDRATE; SODIUM BENZOATE; WATER; DIDECYLDIMONIUM CHLORIDE; PROPYLENE GLYCOL; PHENOXYETHANOL; IODOPROPYNYL BUTYLCARBAMATE; GLYCERIN; ALOE VERA LEAF JUICE; CHAMOMILE; LONICERA JAPONICA FLOWER; HYALURONATE SODIUM; CITRIC ACID MONOHYDRATE; SODIUM BENZOATE

fomin® mini Hand Sanitizer Wipes VARIETY PACK

Active Ingredient:

Benzalkonium Chloride 0.1%

Purpose:

Antiseptic

Use:

• For handwashing to decrease bacteria on the skin.

Warnings:

• For external use only. • Flammable.

Keep out of reach of children.

Directions:

• Open packet and wipe hands thoroughly for at least 15 seconds. Allow to dry without wiping.

Inactive Ingredients:

Water (Aqua), Didecyldimonium Chloride, Propylene Glycol, Phenoxyethanol, Iodopropynyl Butylcarbamate, Glycerin, Aloe Barbadensis Leaf Juice, Chamomilla Recutita (Matricaria) Flower Extract, Lonicera Japonica (Honeysuckle) Flower Extract, Sodium Hyaluronate, Citric Acid, Fragrance, Sodium Benzoate

KILLS 99.9% OF GERMS

ALCOHOL FREE FORMULA

Clean Hands, Wherever You Go

HYALURONIC ACID

ALOE VERA

Packed With Fresh Scents

2 X MELON POP

2 X COCO-NILLA BLISS

2X FRAGRANCE FREE

Clean For You & Our Planet

Stay fresh and protected wherever you go with Fomin Hand Sanitizer Wipes. Designed for effective cleansing, these wipes eliminate 99.9% of germs and bacteria while keeping your hands soft and nourished. Unlike harsh sanitizers, our gentle, alcohol-free formula won't dry out your skin, making them ideal for all skin types.

99.9% GERM PROTECTION

HYPOALLERGENIC

DERMATOLOGIST-TESTED & BABY-SAFE

When You Need It The Most

GYM KIDS
PURSE TRAVEL

Safe for Children

DISCLAIMER: For external use only (including intimate areas). Avoid contact with eyes; if contact occurs, rinse thoroughly with water. Do not apply to broken or irritated skin. Discontinue use if irritation or redness appears. Keep out of reach of children. Do not flush wipes down the toilet - dispose responsibly. STORAGE: Store in a cool, dry place. Keep sachets sealed until use.
QUESTIONS: For questions and general information visit us at fominsoap.com/contact

@fominsoap fominsoap.com

Manufactured for Petra Brands Co., Limited.
Distributed by Fomin LLC, Wilmington, DE 19801, USA.
Designed in USA. Made in PRC
www.fominsoap.com

1% FOR THE PLANET

LEAPING BUNNY CERTIFIED

PLASTIC BANK CERTIFIED

OEKO-TEX® CERTIFIED ORGANIC COTTON

HYDRATING

Plant-Based Wipes